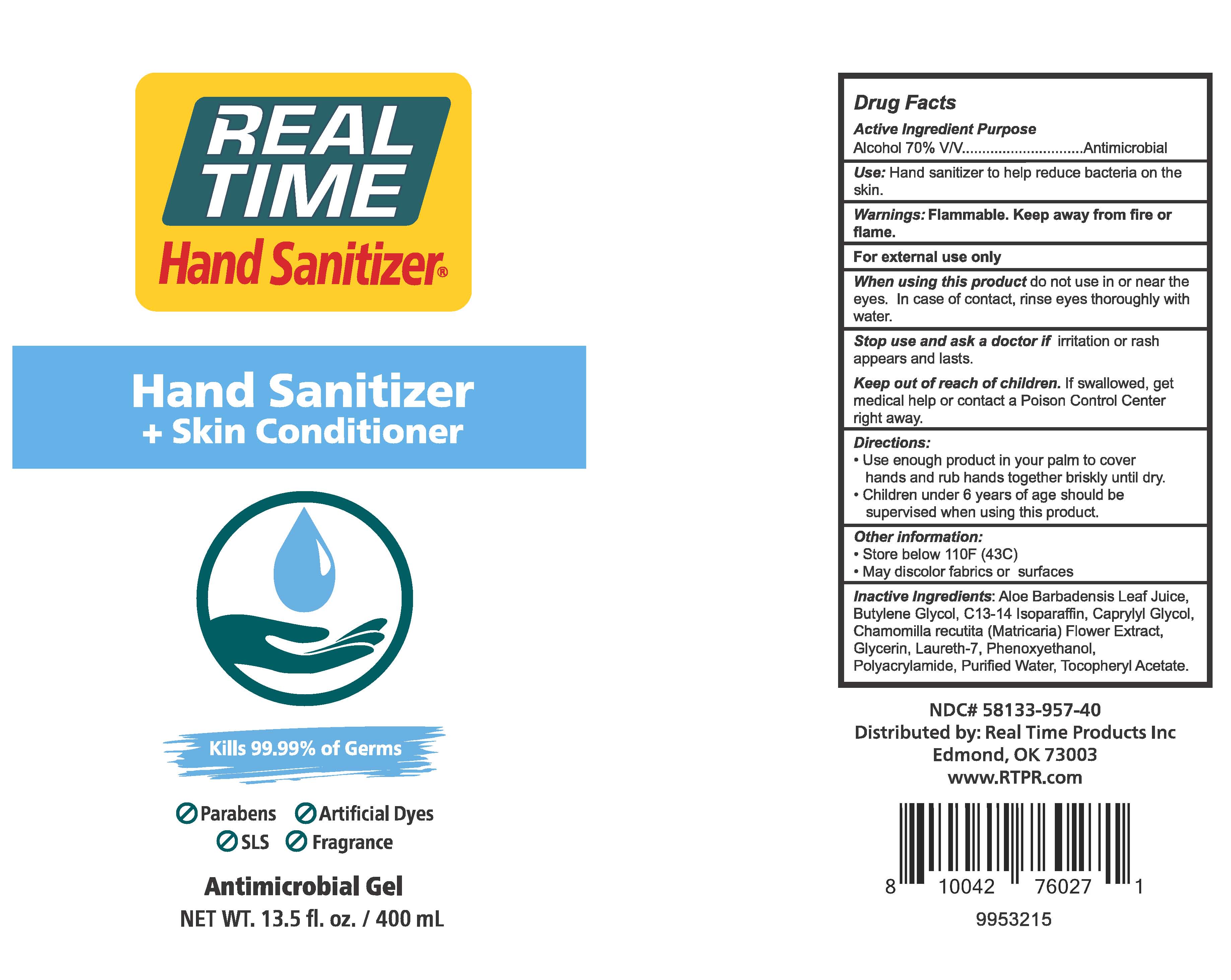 DRUG LABEL: Real Time Hand Sanitizer 70% Alcohol
NDC: 58133-957 | Form: GEL
Manufacturer: Cosmetic Specialty Labs, Inc.
Category: otc | Type: HUMAN OTC DRUG LABEL
Date: 20200713

ACTIVE INGREDIENTS: ALCOHOL 70 mL/100 mL
INACTIVE INGREDIENTS: C13-14 ISOPARAFFIN; .ALPHA.-TOCOPHEROL ACETATE; BUTYLENE GLYCOL; MATRICARIA CHAMOMILLA FLOWERING TOP OIL; LAURETH-7; GLYCERIN; WATER; POLYACRYLAMIDE (10000 MW); ALOE VERA LEAF; CAPRYLYL GLYCOL; PHENOXYETHANOL

Real Time Hand Sanitizer

Active Ingredient

Alcohol 70% v/v

Purpose

Antimicrobial

Use

Hand sanitizer to help reduce bacteria on the skin.

Warnings

For external use only.

Flammable - Keep away from fire or flame.

When using this product

do not use in or near the eyes. In case of contact, rinse eyes thoroughly with water.

Stop use and ask a doctor if

irritation or rash appears and lasts.

Keep out of reach of children

If swallowed, get medical help or contact a Poison Control Center right away.

Directions

• Use enough product in your palm to cover
hands and rub hands together briskly until dry.
• Children under 6 years of age should be
supervised when using this product.

Other information

- Do not store above 110°F (43°C)
- May discolor fabrics or surfaces

Inactive Ingredients

Aloe Barbadensis Leaf Juice,
Butylene Glycol, C13-14 Isoparaffin, Caprylyl Glycol,
Chamomilla recutita (Matricaria) Flower Extract,
Glycerin, Laureth-7, Phenoxyethanol,
Polyacrylamide, Purified Water, Tocopheryl Acetate.